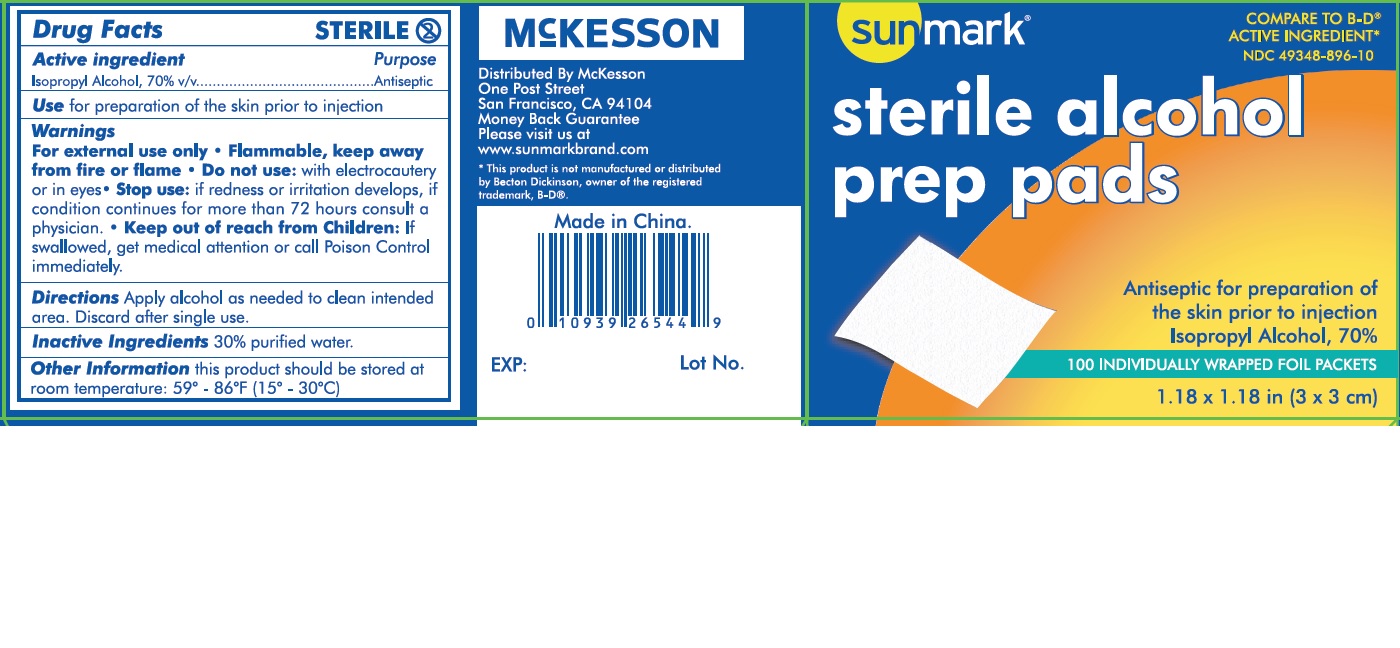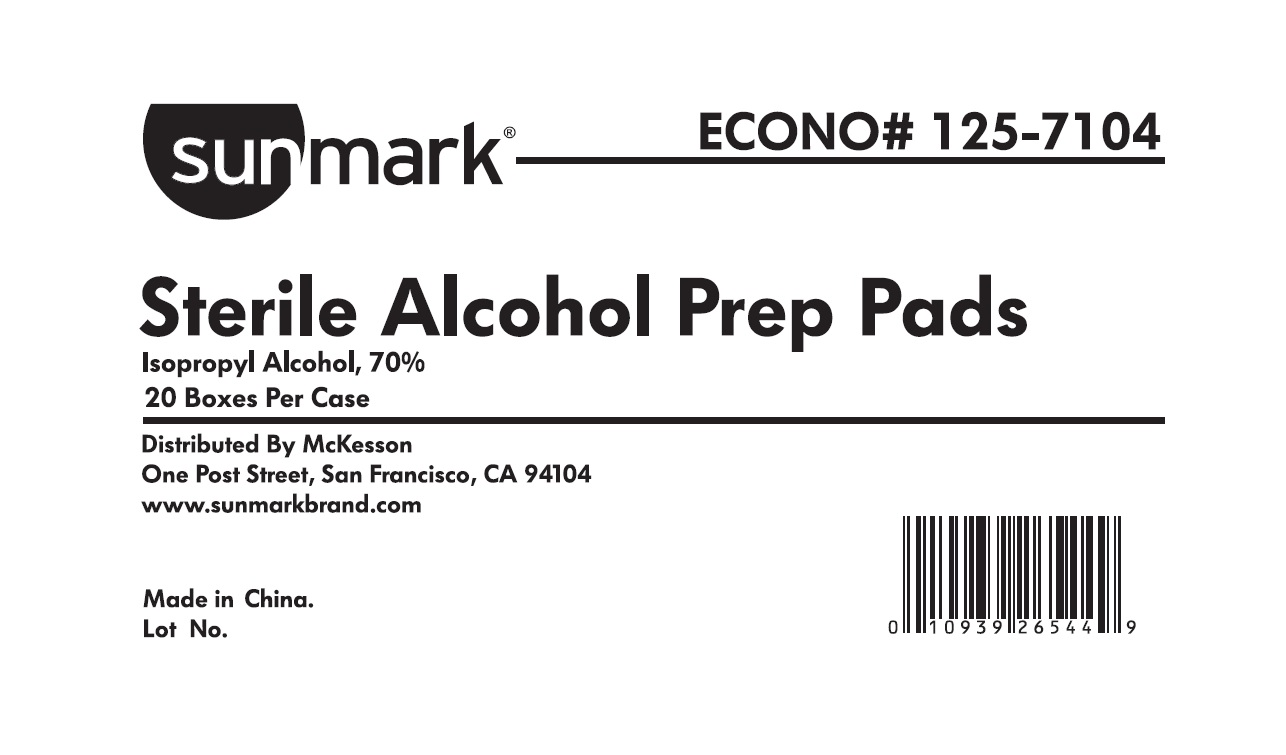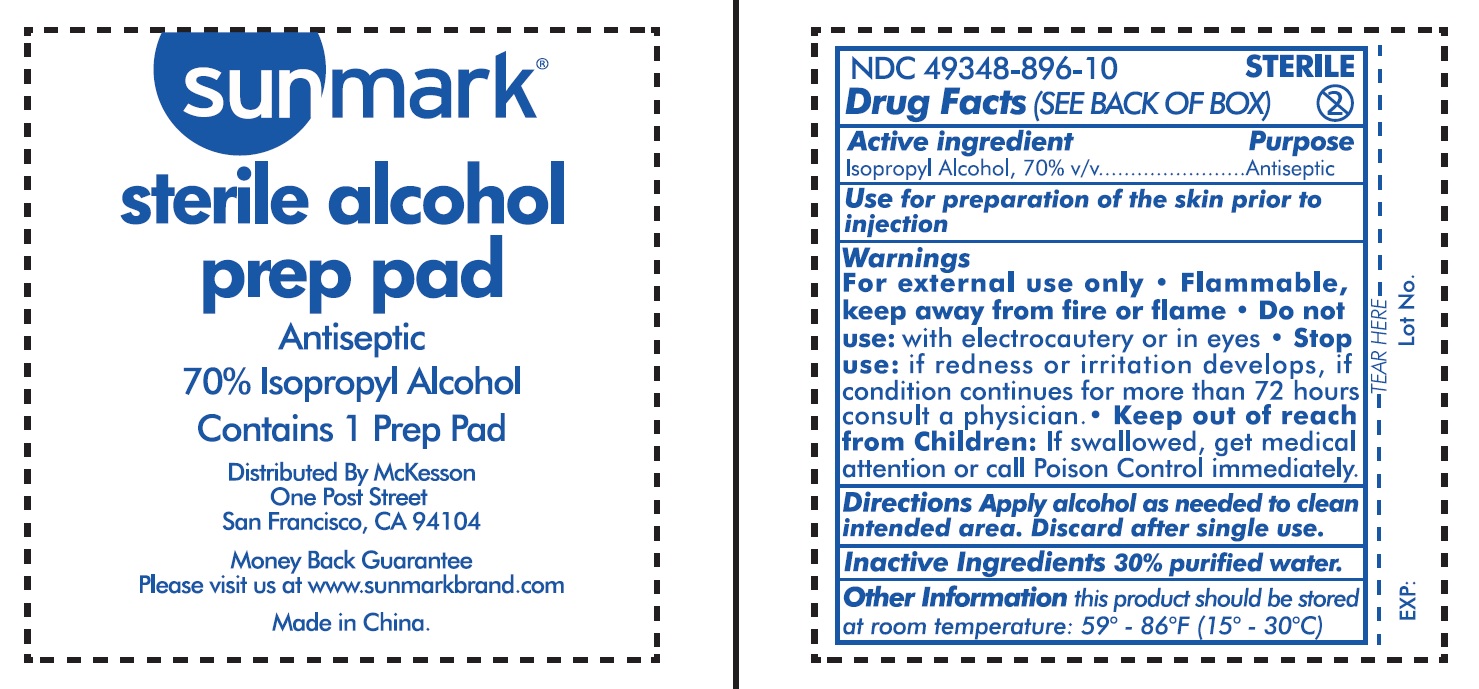 DRUG LABEL: Isopropyl Alcohol
NDC: 49348-896 | Form: SWAB
Manufacturer: Strategic Sourcing Services LLC
Category: otc | Type: HUMAN OTC DRUG LABEL
Date: 20240307

ACTIVE INGREDIENTS: ISOPROPYL ALCOHOL 0.7 mL/1 1
INACTIVE INGREDIENTS: WATER

Isopropyl Alcohol

Drug Facts

Active ingredient

Isopropyl Alcohol, 70% v/v

Purpose

Antiseptic

INDICATIONS AND USAGE

Use for preparation of the skin prior to injection

Warnings

For external use only

- Flammable, keep away from fire or flame

- Do not use: with electrocautery or in eyes

- Stop use: if redness or irritation develops, if condition continues for more than 72 hours consult a physician.

KEEP OUT OF REACH OF CHILDREN

- Keep out of reach from Children: If swallowed, get medical attention or call Poison Control immediately.

Directions

Apply alcohol as needed to clean intended area.

Discard after single use.

Inactive Ingredients

30% purified water.

Other Information

this product should be stored at room temperature: 59° - 86°F(15° - 30°C)

Principal Display Panel – Pad Label

49348-896-10

sunmark®

Alcohol Prep Pad

STERILE∙ Antiseptic 70% Isopropyl Alcohol Contains 1 Prep Pad

MFR # 125-7104

Distributed By McKesson

One Post Street San Francisco, CA 94104

Money Back Guarantee Please visit us at www.sunmarkbrand.com

Made in China.

Principal Display Panel – Carton Label

49348-896-10

sunmark ®

Alcohol Prep Pad

STERILE ∙ Antiseptic 70% Isopropyl Alcohol Contains 1 Prep Pad

MFR # 125-7104

Distributed By McKesson

One Post Street San Francisco, CA 94104

Money Back Guarantee Please visit us at www.sunmarkbrand.com

Made in China.

Box label

49348-896-10

sunmark ®

Alcohol Prep Pad

STERILE ∙ Antiseptic 70% Isopropyl Alcohol Contains 1 Prep Pad

MFR # 125-7104

Distributed By McKesson

One Post Street San Francisco, CA 94104

Money Back Guarantee Please visit us at www.sunmarkbrand.com

Made in China.